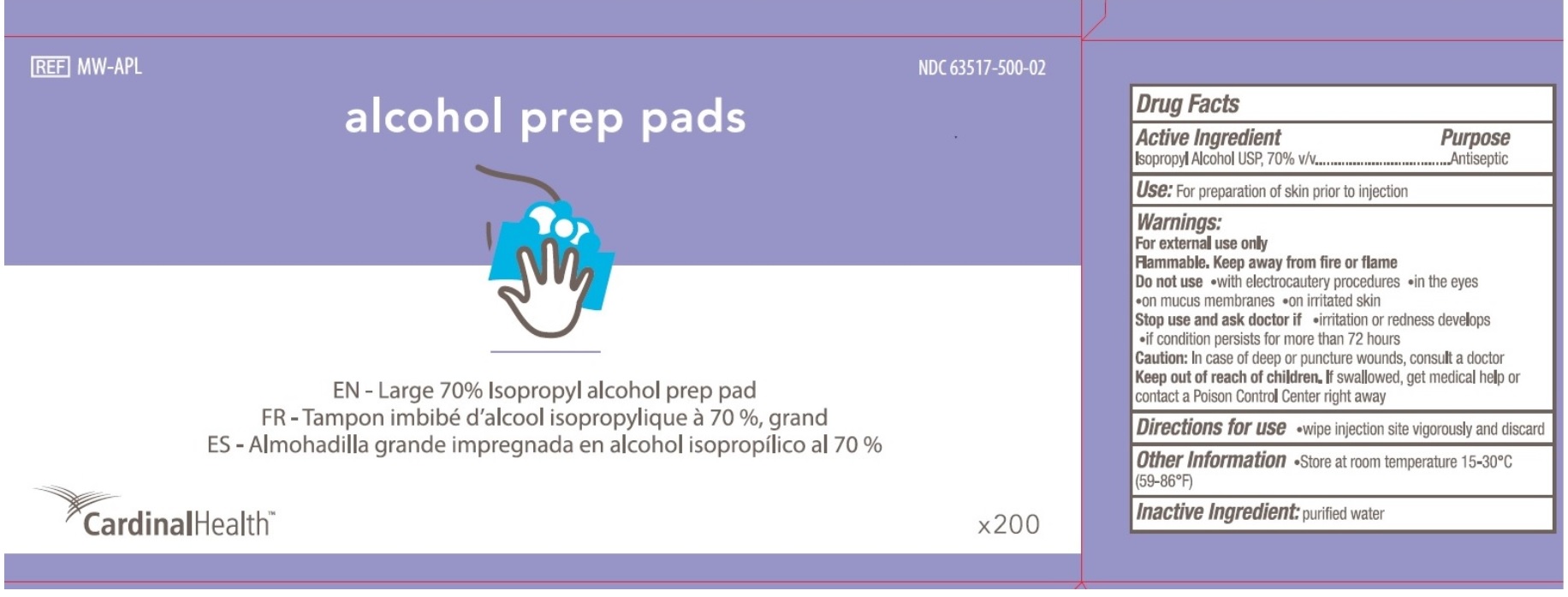 DRUG LABEL: Alcohol Prep Pads
NDC: 63517-500 | Form: SWAB
Manufacturer: Cardinal Health
Category: otc | Type: HUMAN OTC DRUG LABEL
Date: 20251023

ACTIVE INGREDIENTS: ISOPROPYL ALCOHOL 70 mL/100 mL
INACTIVE INGREDIENTS: WATER

Cardinal Large Alcohol Prep Pads

Active Ingredients

Isopropyl Alcohol USP, 70% v/v

Purpose

Antiseptic

Uses

For preparation of skin prior to injection

Warnings

For external use only

Flammable. Keep away from fire or flame

Do not use

- with electrocautery procedures
- in the eyes
- on mucus membrane
- on irritated skin

Stop use and ask doctor if

- irritation or redness develops
- if condition persists for more than 72 hours

Caution

In case of deep or punctured wounds, consult a doctor

Keep out of reach of children

If swallowed, get medical help or contact a Poison Control Center right away

Directions for use

- wipe injection site vigorously and discard

Other Information

- Store at room temperature 15-30⁰C (59-86⁰F)

Inactive Ingredient

purified water

Principal Display Panel

REF MW-APL

NDC 63517-500-02

alcohol prep pads

EN - Large 70% Isopropyl alcohol prep pad

FR - Tampon imbibe'd'alcool isopropylique a 70%, grand

ES - Almohadilla grande impregnada en alcohol isopropilico al 70%

CardinalHealth

x200